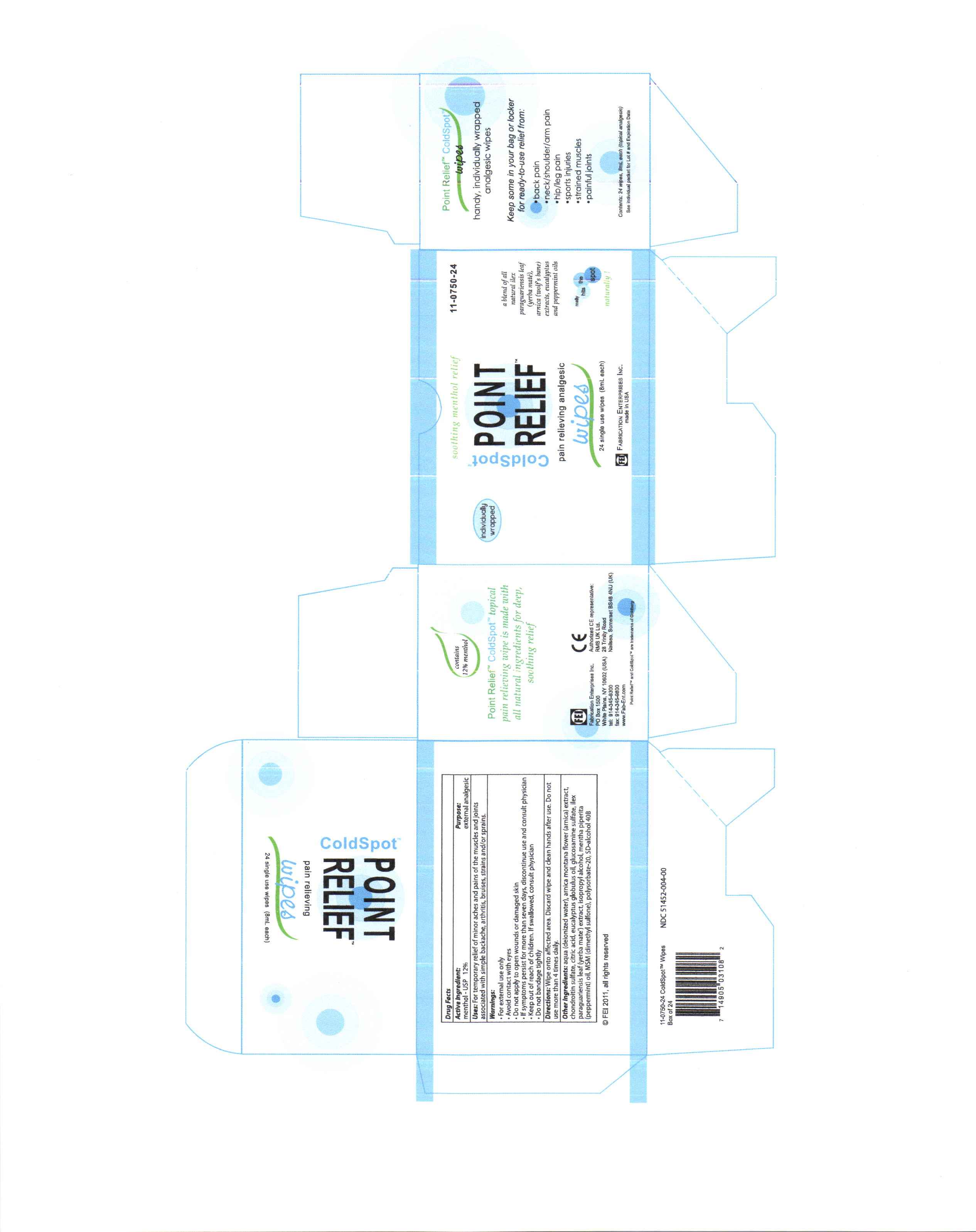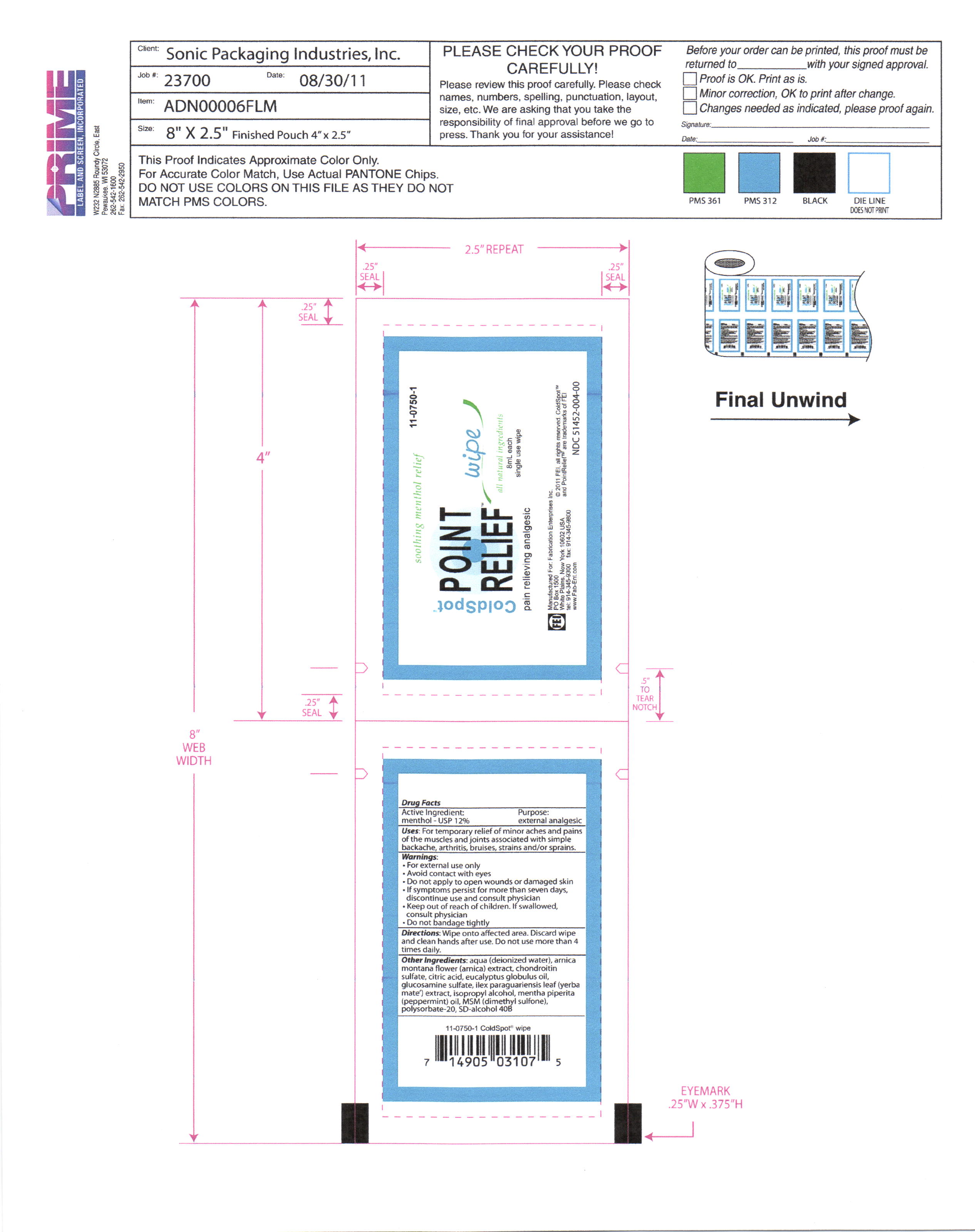 DRUG LABEL: Cold Spot
NDC: 51452-004 | Form: SWAB
Manufacturer: Fabrication Enterprises, inc. 
Category: otc | Type: HUMAN OTC DRUG LABEL
Date: 20111014

ACTIVE INGREDIENTS: Menthol .96 mL/8 mL
INACTIVE INGREDIENTS: WATER; ARNICA MONTANA FLOWER; BOSWELLIA SERRATA RESIN OIL; BROMELAINS; alcohol; Eucalyptus Globulus leaf; ILEX PARAGUARIENSIS LEAF; Peppermint Oil; Dimethyl Sulfone; Chondroitin sulfate (bovine); Citric Acid; Isopropyl Alcohol; polysorbate 20

coldspot point relief

ACTIVE INGREDIENT

menthol - usp 12%

INACTIVE INGREDIENT

aqua (deionized water), arnica montana flower (arnica) extract, chondroitin sulfate, citric acid, eucalyptus globulus oil, glucosamine sulfate,ilex paraguariensis leaf (yerba mate) extract, isopropyl alcohol, menth piperita (pepperment) oil, MSM (dimethyl sulfone) polysorbate-20, SD-alcohol 40B, triethanolamine

Keep out of reach of children. If swallowed, consult physician.

WARNINGS

for external use only

avoid contact with eyes

do not apply to open wounds or damaged skin

if symptoms persist for more than seven days, discontinue use and consult physician

keep out of reach of children. if swallowed, consult physician

do not bandage tightly

INDICATIONS AND USAGE

for temporary relief of minor aches and pains of the muscles and joints associated with simple backache, arthritis, bruises, strains and/or sprains.

DOSAGE AND ADMINISTRATION

wipe onto affected area. discard wipe and clean hands after use. do not use more than four times per day.

PURPOSE

For temporary relief of minor aches and pains of the muscles and joints associated with simple backache, arthritis, bruises, strains and/or sprains.

PACKAGE LABEL

cold spot point relief wipes